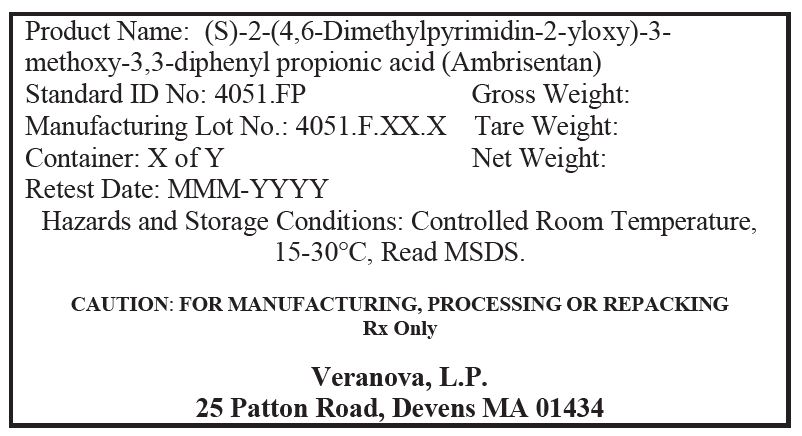 DRUG LABEL: Ambrisentan
NDC: 50137-4051 | Form: POWDER
Manufacturer: Veranova, L.P.
Category: other | Type: BULK INGREDIENT
Date: 20260106

ACTIVE INGREDIENTS: AMBRISENTAN 1 kg/1 kg

Ambrisentan (4051.F)